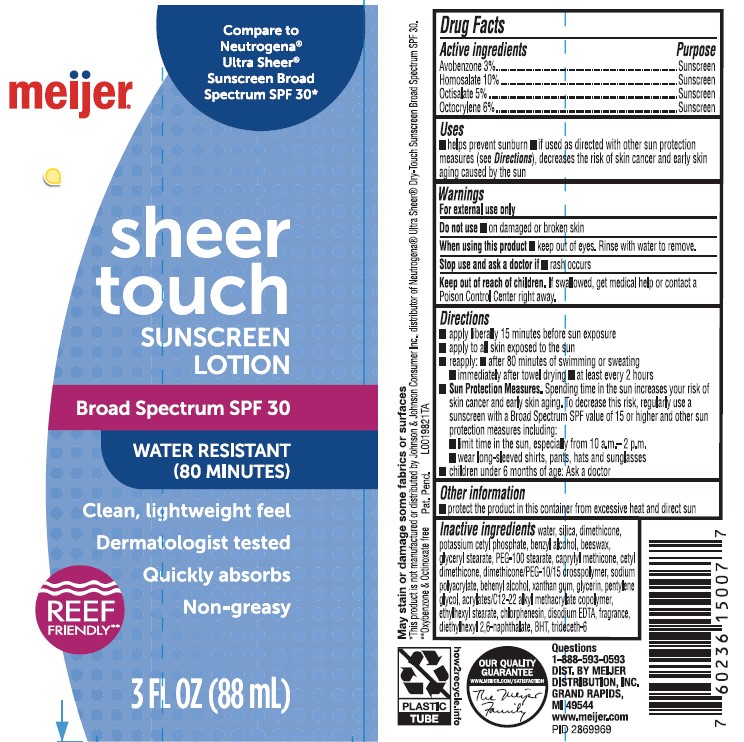 DRUG LABEL: Sunscreen
NDC: 79481-0914 | Form: LOTION
Manufacturer: Meijer, Inc.
Category: otc | Type: HUMAN OTC DRUG LABEL
Date: 20260220

ACTIVE INGREDIENTS: AVOBENZONE 30 mg/1 mL; HOMOSALATE 100 mg/1 mL; OCTISALATE 50 mg/1 mL; OCTOCRYLENE 60 mg/1 mL
INACTIVE INGREDIENTS: ETHYLHEXYL STEARATE; CHLORPHENESIN; EDETATE DISODIUM ANHYDROUS; DIETHYLHEXYL 2,6-NAPHTHALATE; BUTYLATED HYDROXYTOLUENE; TRIDECETH-6; WATER; SILICON DIOXIDE; DIMETHICONE; POTASSIUM CETYL PHOSPHATE; BENZYL ALCOHOL; YELLOW WAX; GLYCERYL MONOSTEARATE; PEG-100 STEARATE; CAPRYLYL TRISILOXANE; CETYL DIMETHICONE 150; DIMETHICONE PEG-10 PHOSPHATE; SODIUM POLYACRYLATE (8000 MW); DOCOSANOL; XANTHAN GUM; GLYCERIN; PENTYLENE GLYCOL; ALLYL METHACRYLATE

Meijer 914.000/914AA
Sheer Touch Sunscreen SPF 30

active ingredients

Avobenzone 3%

Homosalate 10%

Octisalate 5%

Octocrylene 6%

Purpose

Sunscreen

Uses

- helps prevent sunburn
- if used as directed with other sun protection measures (See Directions), decreases the risk of skin cancer and early skin aging caused by the sun

Warnings

For external use only

Do not use

- on damaged or broken skin

When using this product

- keep out of eyes. Rinse with water to remove.

Stop use and ask a doctor if

- rash occurs

Keep out of reach of children.

If swallowed, get medical help or contact a Poison Control right away.

Directions

- apply liberaly 15 minutes before sun exposure
- apply to all skin exposed to the sun
- reapply:
- after 80 minutes of swimming or sweating
- immediately after towel drying
- at least every 2 hours
- Sun Protection Measures. Spending time in the sun increases your risk of skin cancer and early skin aging. To decrease this risk, regularly use a sunscreen with Broad Spectrum SPF value of 15 or higher and other sun protection measures including:
- limit time in the sun, especialy from 10 a.m. -2 p.m.
- wear long-sleeved shirts, pants, hats and sunglasses
- children under 6 months of age: Ask a doctor

Other information

- protect the product in this container from excessive heat and direct sun

inactive ingredients

water, silica, dimethicone, potassium cetyl phosphate, benzyl alcohol, beeswax, glyceryl stearate, PEG-100 stearate, caprylyl methicone, cetyl dimethicone, dimethicone/PEG-10/15 crosspolymer, sodium polyacrylate, behenyl alcohol, xanthan gum, glycerin, pentylene glycol, acrylates/C12-22 alkyl methacrylate copolymer, ethylhexyl stearate, chlorphenesin, disodium EDTA, fragrance, diethylhexyl 2,6-naphthalate, BHT, trideceth-6

Disclaimer

May stain or damage some fabrics or surfaces

*This product is not manufactured or distributed by Johnson & Johnson Consumer Inc., distributor of NeutrogenaUltra Sheer Dry-Touch Sunscreen Broad Spectrum SPF 30.

**Ozybenzone & Octinoxate free

Adverse reaction

Questions 1-888-593-0593

DISTRIBUTED BY MEIJER

DISTRIBUTION, INC.

GRAND RAPIDS, MI 49544

www.meijer.com

OUR QUALITY GUARANTEE

WWW.MEIJER.COM/SATISFACTION

The Meijer Family

PLASTIC TUBE

how2recycle.info

principal display panel

Compare to Neutrogena®Ultra Sheer®Sunscreen Broad Spectrum SPF 30*

meijer®

sheer

touch

SUNSCREEN

LOTION

Broad Spectrum SPF 30

WATER RESISTANT (80 MINUTES)

Clean, Lightweight feel

Dermatologist tested

Quickly absorbs

Non-greasy

REEF FRIENDLY**

3 FL OZ (88 mL)